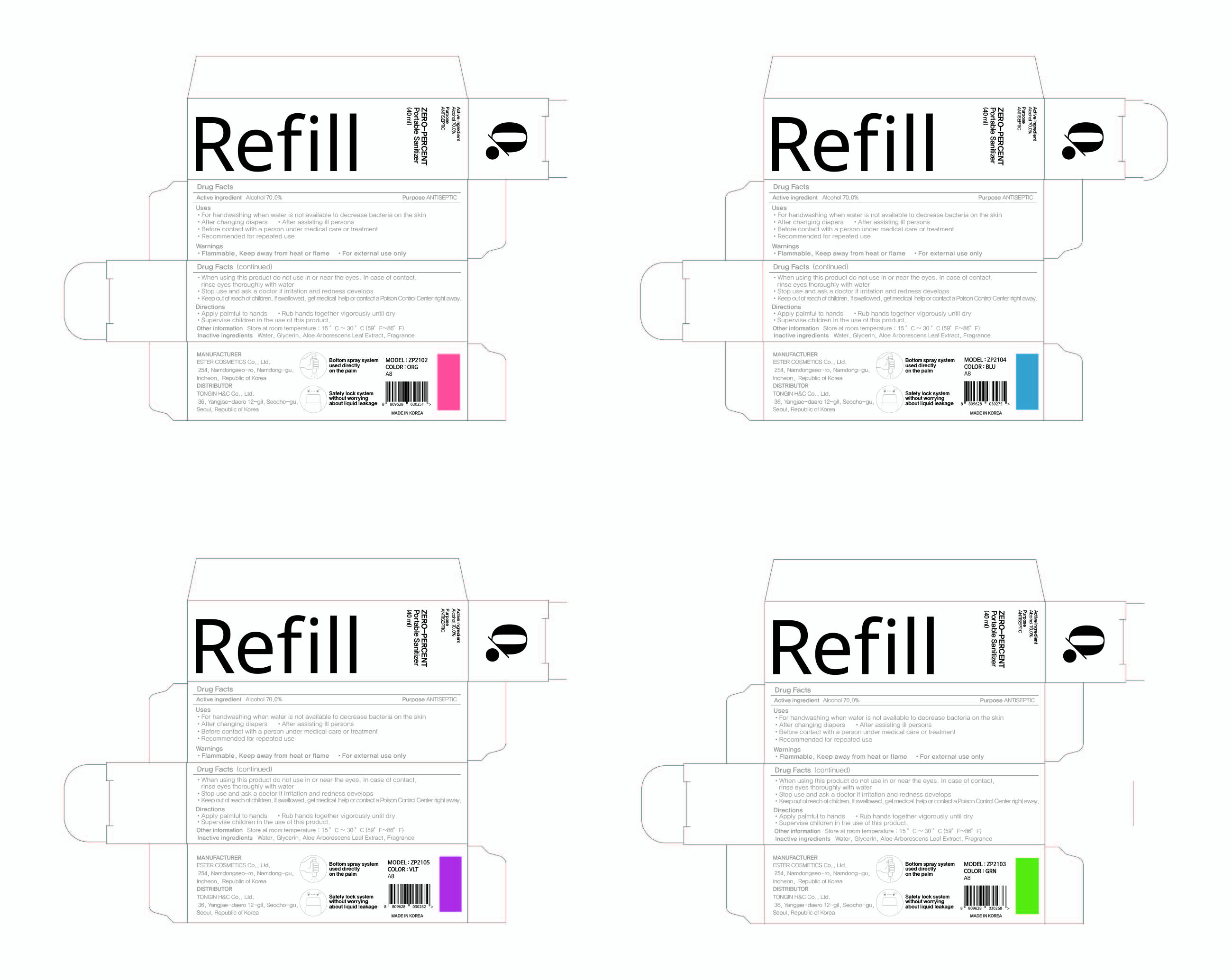 DRUG LABEL: ZERO-PERCENT Portable Sanitizer Refill
NDC: 74004-043 | Form: LIQUID
Manufacturer: Ester Co., Ltd.
Category: otc | Type: HUMAN OTC DRUG LABEL
Date: 20201006

ACTIVE INGREDIENTS: ALCOHOL 28 mL/40 mL
INACTIVE INGREDIENTS: WATER; GLYCERIN; ALOE ARBORESCENS LEAF

[3] ZERO-PERCENT Portable Sanitizer Refill (Fragrance)
74004-043-02
Box, 4 colors